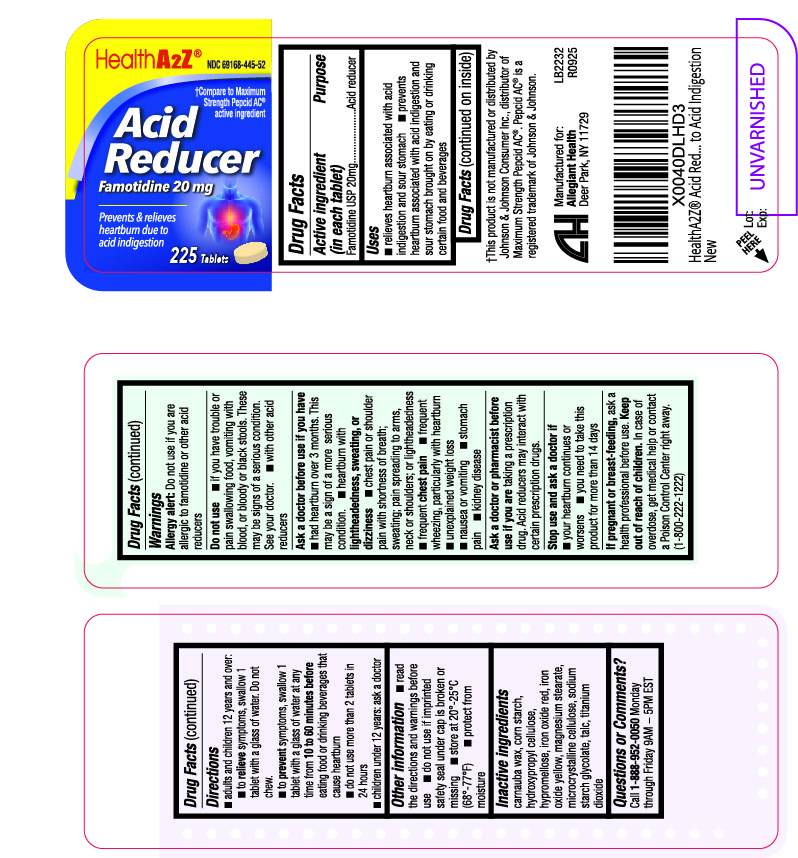 DRUG LABEL: Acid Reducer
NDC: 69168-445 | Form: TABLET
Manufacturer: Allegiant Health
Category: otc | Type: HUMAN OTC DRUG LABEL
Date: 20241030

ACTIVE INGREDIENTS: FAMOTIDINE 20 mg/1 1
INACTIVE INGREDIENTS: CARNAUBA WAX; STARCH, CORN; HYDROXYPROPYL CELLULOSE, UNSPECIFIED; HYPROMELLOSE, UNSPECIFIED; FERRIC OXIDE RED; FERRIC OXIDE YELLOW; MAGNESIUM STEARATE

445 - Acid Reducer

Active ingredient(s)

Famotidine USP 20 mg

Purpose

Acid reducer

Use(s)

- relieves heartburn associated with acid indigestion and sour stomach
- prevents heartburn associated with acid indigestion and sour stomach brought on by eating or
  drinking certain food and beverages

Warnings

Allergy alert: Do not use if you are allergic to famotidine or other acid reducers

Do not use

- if you have trouble or pain swallowing food, vomiting with
  blood, or bloody or black stools. These may be signs of a serious condition. See your doctor.
- with other acid reducers

Ask a doctor before use if

you have

- had heartburn over 3 months. This may be a sign of a more serious
  condition.
- heartburn with lightheadedness, sweating, or dizziness
- chest pain or shoulder pain with shortness of breath; sweating; pain spreading to arms,
  neck or shoulders; or lightheadedness
- frequent chest pain
- frequent wheezing, particularly with heartburn
- explained weight loss
- nausea or vomiting
- stomach pain
- kidney disease

Ask a doctor or pharmacist before use if

you are taking a prescription drug. Acid reducers may interact with certain prescription drugs.

Stop use and ask a doctor if

- your heartburn continues or worsens
- you need to take this product for more than 14 days

If pregnant or breastfeeding,

ask a health professional before use.

Keep out of reach of children

In case of overdose, get medical help or contact a Poison Control Center right
away. (1-800-222-1222)

Directions

adults and children 12 years and over:

- to relieve symptoms, swallow 1 tablet with a glass of water. Do not chew.
- to prevent symptoms, swallow 1 tablet with a glass of water at any
  time from 10 to 60 minutes before eating food or drinking beverages that
  cause heartburn
- do not use more than 2 tablets in 24 hours

children under 12 years: ask a doctor

Other information

- read the directions and warnings before use
- do not use if imprinted safety seal under cap is broken or
  missing n store at 20°-25°C (68°-77°F)
- protect from moisture

Inactive ingredients

carnauba wax, corn starch, hydroxypropyl cellulose,
hypromellose, iron oxide red, iron oxide yellow, magnesium stearate, microcrystalline
cellulose, sodium starch glycolate, talc, titanium dioxide

Questions/Comments

Call 1-888-952-0050 Monday through Friday
9AM − 5PM EST

Principal Display Panel

Acid Reducer